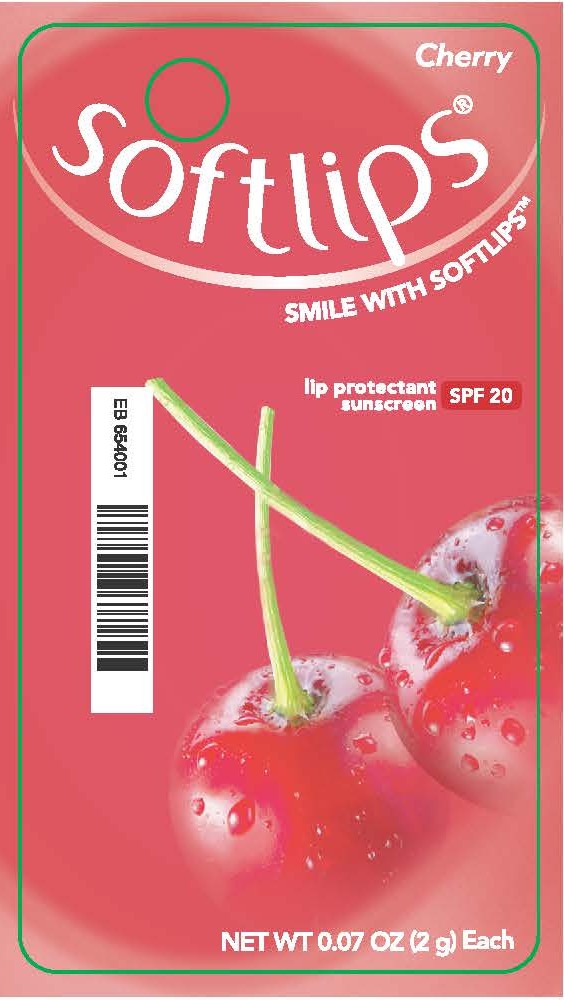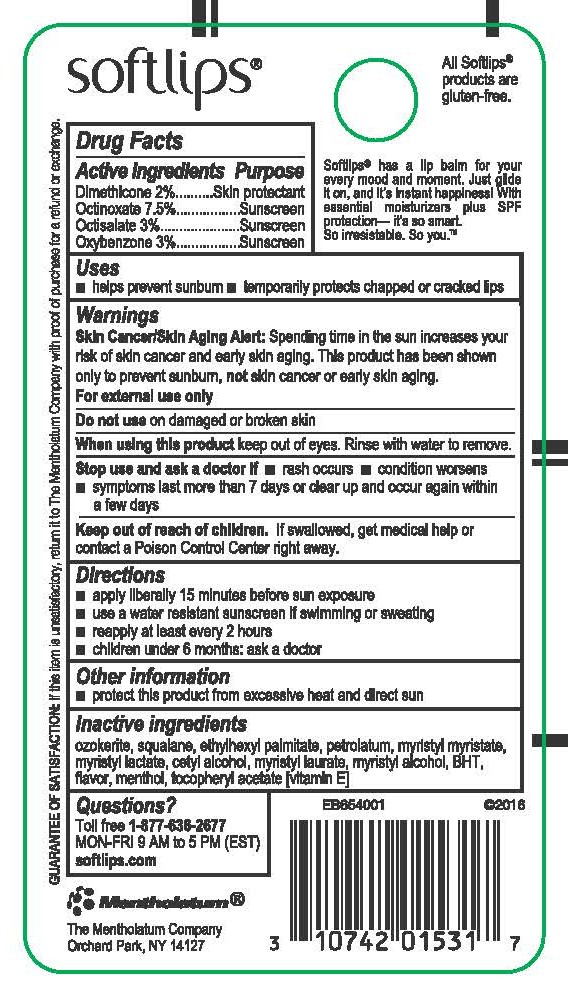 DRUG LABEL: Softlips
NDC: 10742-8512 | Form: OINTMENT
Manufacturer: The Mentholatum Company
Category: otc | Type: HUMAN OTC DRUG LABEL
Date: 20251204

ACTIVE INGREDIENTS: DIMETHICONE 20 mg/1 g; OCTINOXATE 75 mg/1 g; OCTISALATE 30 mg/1 g; OXYBENZONE 30 mg/1 g
INACTIVE INGREDIENTS: CERESIN; SQUALANE; ETHYLHEXYL PALMITATE; PETROLATUM; MYRISTYL MYRISTATE; MYRISTYL LACTATE; CETYL ALCOHOL; MYRISTYL LAURATE; MYRISTYL ALCOHOL; BUTYLATED HYDROXYTOLUENE; MENTHOL, UNSPECIFIED FORM; .ALPHA.-TOCOPHEROL

Drug Facts - Softlips Cherry SPF 20

Active ingredients

Dimethicone 2%

Octinoxate 7.5%

Octisalate 3%

Oxybenzone 3%

Purpose

Dimethicone - Skin protectant

Octinoxate - Sunscreen

Octisalate - Sunscreen

Oxybenzone - Sunscreen

Uses

- helps prevent sunburn
- temporarily protects chapped or cracked lips

Warnings

Skin Cancer/Skin Aging Alert: Spending time in the sun increases your risk of skin cancer and early skin aging. This product has been shown only to prevent sunburn, not skin cancer or early skin aging.

For external use only

Do not use

on damaged or broken skin

When using this product

keep out of eyes. Rinse with water to remove.

Stop use and ask a doctor if

- rash occurs
- condition worsens
- symptoms last more than 7 days or clear up and occur again within a few days

Keep out of reach of children.

If swallowed, get medical help or contact a Poison Control Center right away.

Directions

- apply liberally 15 minutes before sun exposure
- use a water resistant sunscreen if swimming or sweating
- reapply at least every 2 hours
- children under 6 months of age: ask a doctor

Inactive ingredients

ozokerite, squalane, ethylhexyl palmitate, petrolatum, myristyl myristate, myristyl lactate, flavor, cetyl alcohol, myristyl laurate, myristyl alcohol, BHT, menthol, tocopheryl acetate [vitamin E]

Questions?

Toll free 1-877-636-2677 MON-FRI 9 AM to 5 PM (EST) softlips.com